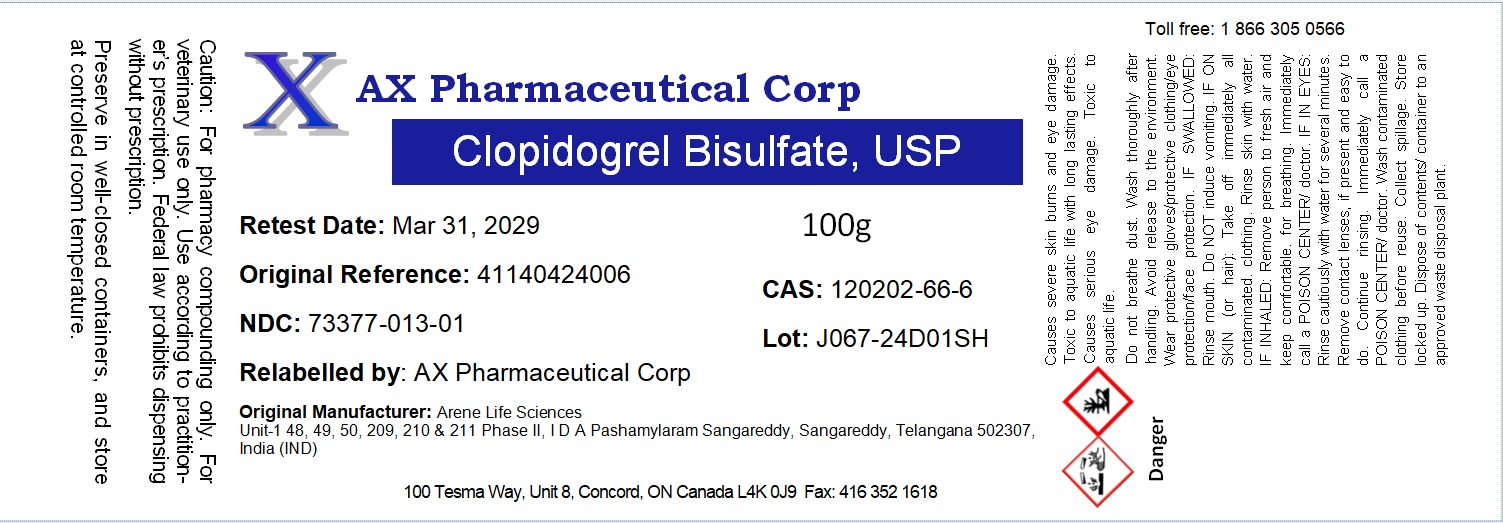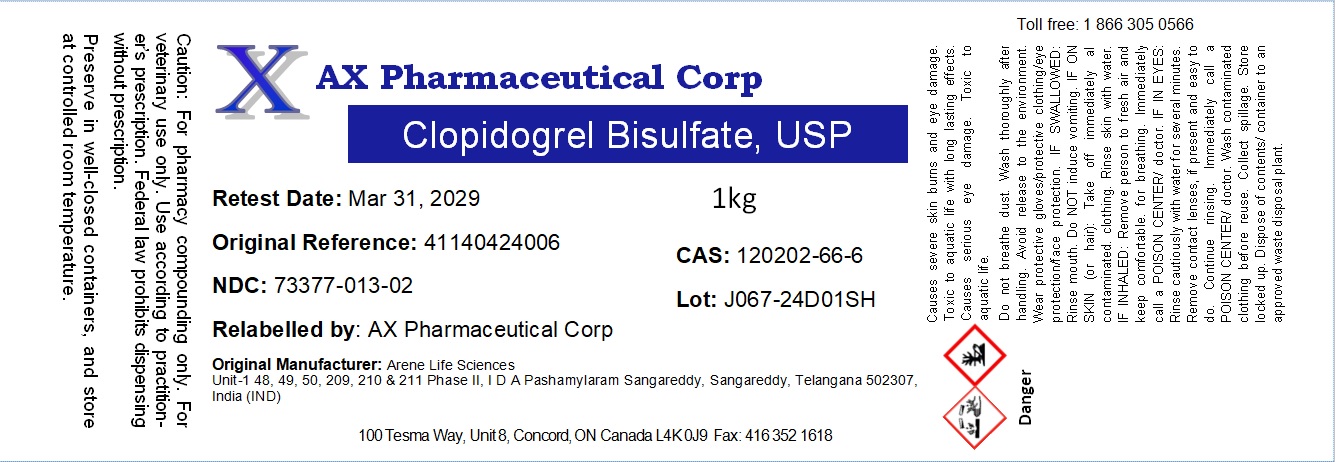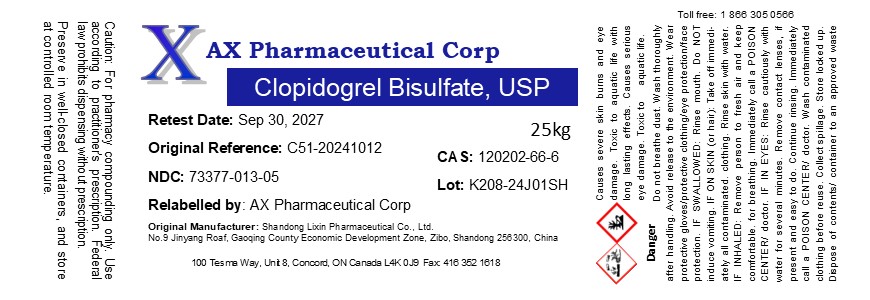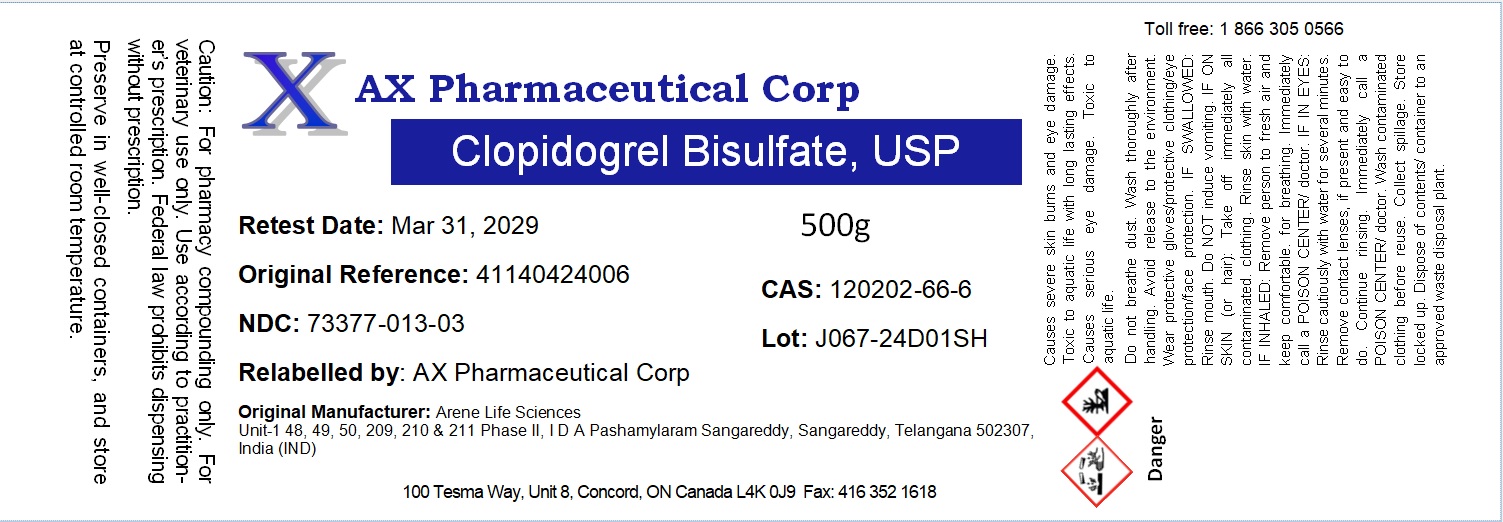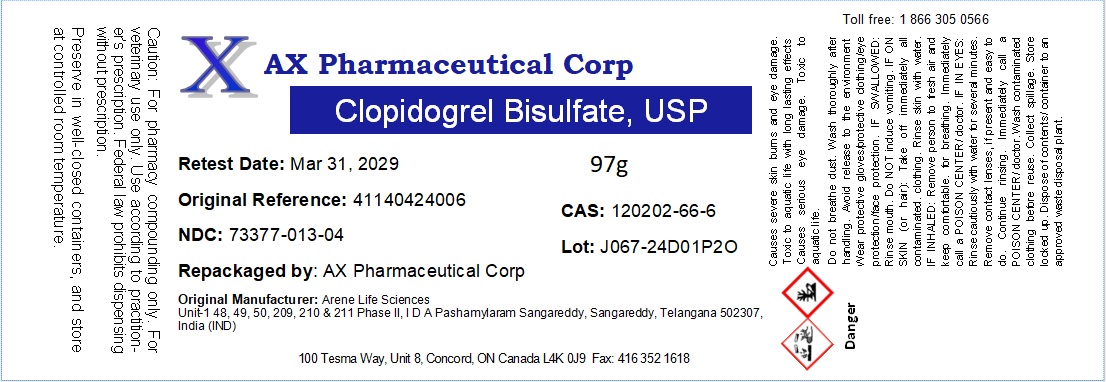 DRUG LABEL: Clopidogrel Bisulfate
NDC: 73377-013 | Form: POWDER
Manufacturer: AX Pharmaceutical Corp
Category: other | Type: BULK INGREDIENT - ANIMAL DRUG
Date: 20250930

ACTIVE INGREDIENTS: CLOPIDOGREL BISULFATE 1 g/1 g

Clopidogrel Bisulfate